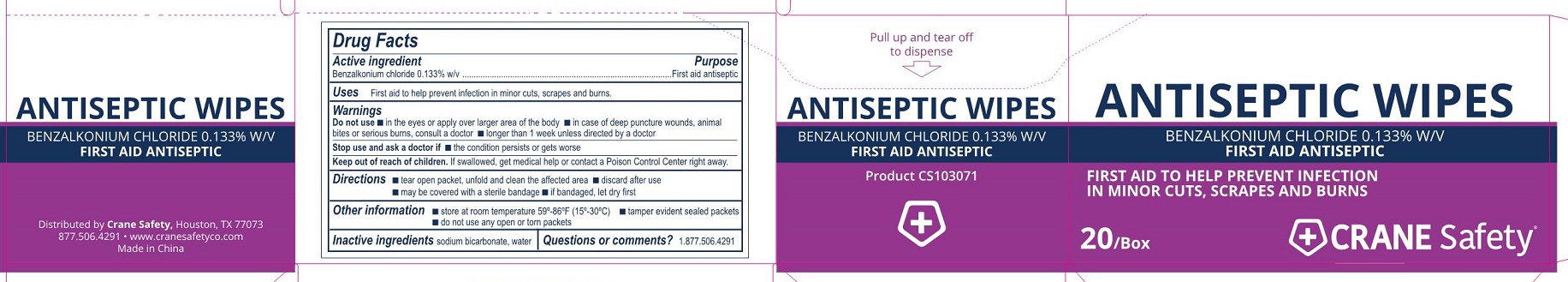 DRUG LABEL: Crane Safety Antiseptic
NDC: 73408-030 | Form: SWAB
Manufacturer: Crane Safety LLC
Category: otc | Type: HUMAN OTC DRUG LABEL
Date: 20230810

ACTIVE INGREDIENTS: BENZALKONIUM CHLORIDE 1.3 mg/1 mL
INACTIVE INGREDIENTS: SODIUM BICARBONATE; WATER

Crane Safety Antiseptic Wipes

Active ingrredient

Benzalkonium chloride 0.133% w/v

Purpose

First aid antiseptic

Uses

First aid to help prevent infection in minor cuts, scrapes, and burns.

Do not use

- in the eyes or over large areas of the body
- in case of deep or puncture woulds, animal bite or serious burns, consult a doctor
- longer than 1 week unless directed by a doctor

Stop use and ask a doctor if

- if the condition persists or gets worse

Keep out of reach of children.

If swallowed, get medical help or contact a Poison Control Center right away.

Directions

- tear open packet, unfold and clean the affected area
- discard after use
- may be covered with a sterile bandage
- if bandaged, let dry first

Other information

- store at room temperature 59-86ºF (15-30ºC)
- tamper evident sealed packets
- do not use any open or torn packets

Inactive ingredients

sodium bicarbonate, water

Questions or comments?

877.506.4291

Crane Safety Antiseptic Wipes Label

Antiseptic Wipes

Benzalonium Chloride 0.133% W/V

First Aid Antiseptic

First Aid to Help Prevent Infection in Minor Cuts, Scrapes and Burns

20/Box

CRANE Safety®

se